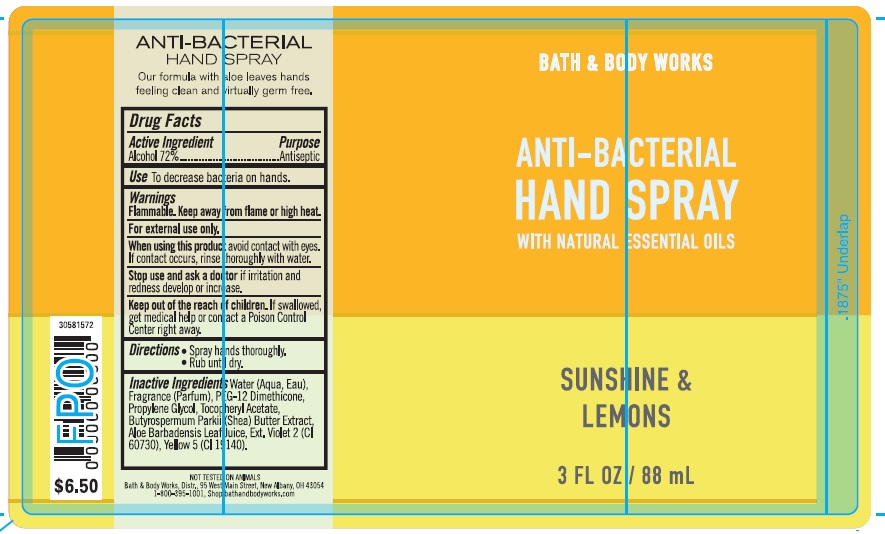 DRUG LABEL: Anti-Bacterial Hand
NDC: 62670-6184 | Form: SPRAY
Manufacturer: Bath & Body Works, Inc.
Category: otc | Type: HUMAN OTC DRUG LABEL
Date: 20211209

ACTIVE INGREDIENTS: ALCOHOL 72 mL/100 mL
INACTIVE INGREDIENTS: WATER

ACTIVE INGREDIENT

Alcohol (72%)

PURPOSE

Antiseptic

USE

To decrease bacteria on skin.

WARNINGS

For external use only.

FLAMMABLE

Keep away from flame or high heat.

WHEN USING THIS PRODUCT

avoid contact with eyes. If contact occurs, rinse thoroughly with water.

STOP USE AND ASK A DOCTOR

if irritation and redness develop.

KEEP OUT OF THE REACH OF CHILDREN

If swallowed, get medical help or contact a Poison Control Center right away.

DIRECTIONS

- Spray hands thoroughly.
- Rub until dry.

INACTIVE INGREDIENTS

Water (Aqua, Eau), Fragrance (Parfum), PEG-12 Dimethicone, Propylene Glycol, Tocopheryl Acetate, Butyrospermum Parkii (Shea) Butter Extract, Aloe Barbadensis Leaf Juice, Ext. Violet 2 (CI 60730), Yellow 5 (CI 19140).

COMPANY INFORMATION

Bath & Body Works, Distr.
Reynoldsburg, Ohio 43068
1-800-395-1001
www.bathandbodyworks.com